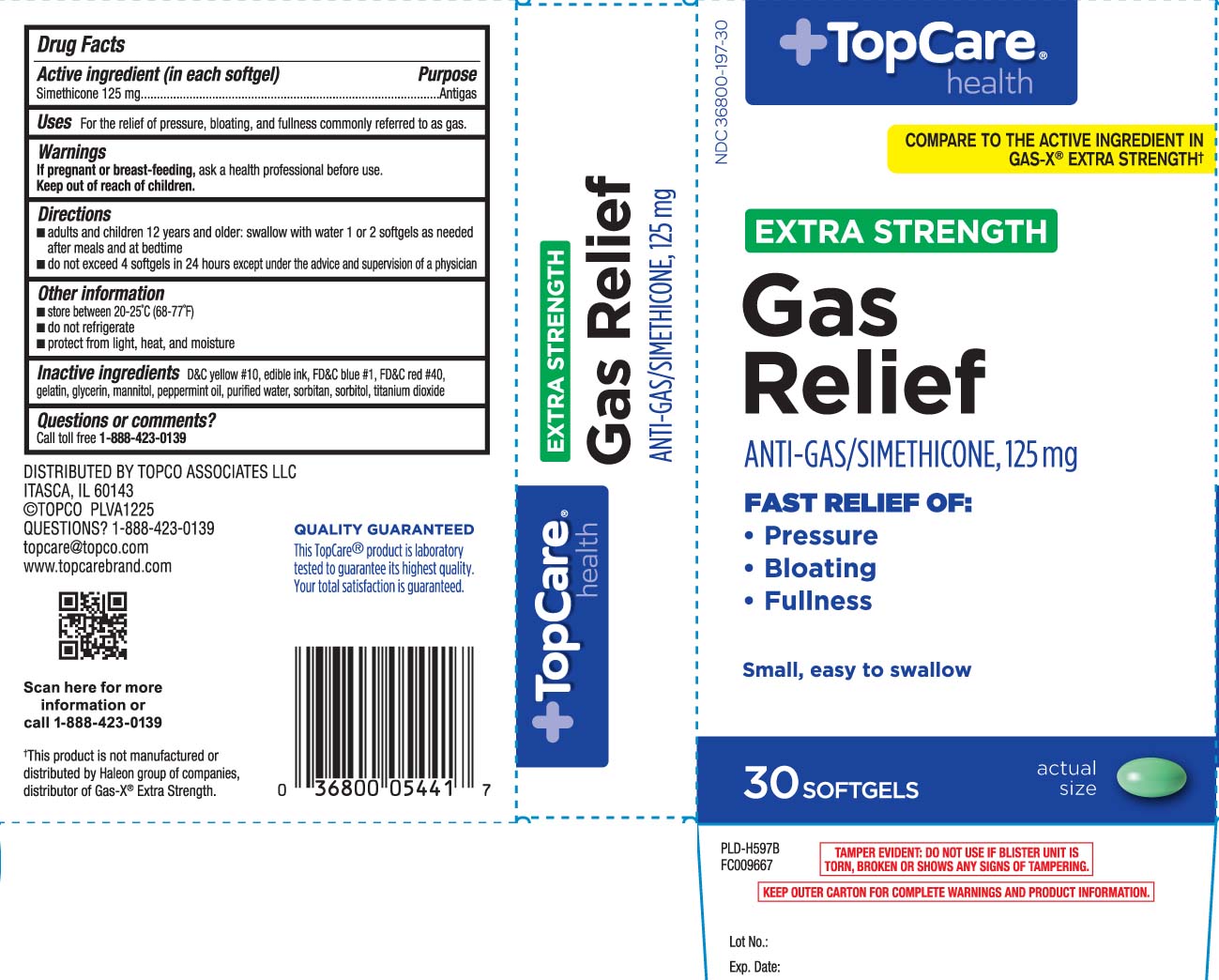 DRUG LABEL: Gas Relief
NDC: 36800-197 | Form: CAPSULE, LIQUID FILLED
Manufacturer: TOP CARE (Topco Associates LLC)
Category: otc | Type: HUMAN OTC DRUG LABEL
Date: 20260302

ACTIVE INGREDIENTS: DIMETHICONE 125 mg/1 1
INACTIVE INGREDIENTS: D&C YELLOW NO. 10; FD&C BLUE NO. 1; FD&C RED NO. 40; GELATIN; GLYCERIN; PEPPERMINT OIL; WATER; SORBITAN; SORBITOL; TITANIUM DIOXIDE; MANNITOL

Drug Facts

Active ingredient (in each softgel)

Simethicone 125 mg

Purpose

Antigas

Uses

For the relief of pressure, bloating, and fullness commonly referred to as gas.

Warnings

If pregnant or breast-feeding,

ask a health professional before use.

Directions

- adults and children 12 years and older: swallow with water 1 or 2 softgels as needed after meals and at bedtime
- do not exceed 4 softgels in 24 hours except under the advice and supervision of a physican

Other information

- store between 20-25°C (68-77°F)
- do not refrigerate
- protect from light, heat, and moisture

Inactive ingredients

D&C yellow #10, edible ink, FD&C blue #1, FD&C red #40, gelatin, glycerin, mannitol, peppermint oil, purified water, sorbitan, sorbitol, titanium dioxide

Questions or comments?

Call toll free 1-888-423-0139

Principal Display Panel

COMPARE TO THE ACTIVE INGREDIENT IN GAS-X® EXTRA STRENGTH†

EXTRA STRENGTH

Gas Relief

ANTI-GAS/SIMETHICONE 125 mg

FAST RELIEF OF:

- Pressure
- Bloating
- Fullness

Small, easy to swallow

SOFTGELS

†This product is not manufactured or distributed by Haleon group of companies, distributor of Gas-X Extra Strength.

TAMPER EVIDENT: DO NOT USE IF BLISTER UNIT IS TORN, BROKEN OR SHOWS ANY SIGNS OF TAMPERING.

KEEP OUTER CARTON FOR COMPLETE WARNINGS AND PRODUCT INFORMATION.

DISTRIBUTED BY TOPCO ASSOCIATES LLC

ITASCA, IL 60143

topcare@topco.com

www.topcarebrand.com

Product Label

TOPCARE HEALTH Extra Strength Gas Relief